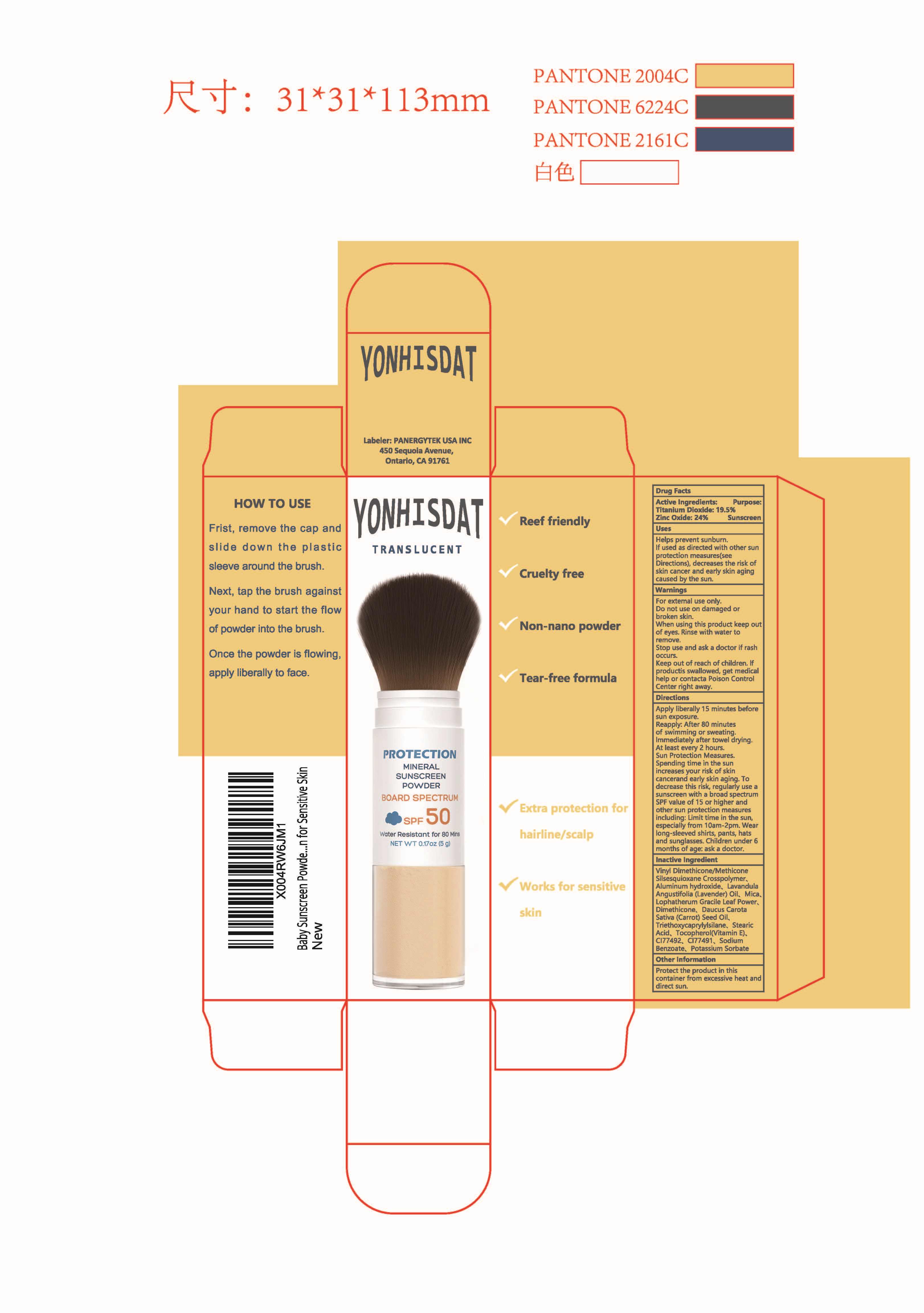 DRUG LABEL: YONHISDAT Sunscreen Powder
NDC: 85950-002 | Form: POWDER
Manufacturer: PANERGYTEK USA INC
Category: otc | Type: HUMAN OTC DRUG LABEL
Date: 20250801

ACTIVE INGREDIENTS: TITANIUM DIOXIDE 19.5 g/100 g; ZINC OXIDE 24 g/100 g
INACTIVE INGREDIENTS: MICA; LAVANDULA ANGUSTIFOLIA (LAVENDER) OIL; VINYL DIMETHICONE/METHICONE SILSESQUIOXANE CROSSPOLYMER; ALUMINUM HYDROXIDE; LOPHATHERUM GRACILE LEAF; POTASSIUM SORBATE; DAUCUS CAROTA SATIVA (CARROT) SEED OIL; TOCOPHEROL; CI 77491; SODIUM BENZOATE; CI 77492; DIMETHICONE; TRIETHOXYCAPRYLYLSILANE; STEARIC ACID

ACTIVE INGREDIENT

TITANIUM DIOXIDE

19.5%

ZINC OXIDE24%

PURPOSE

Sunscreen

WHEN USING

Helps prevent sunbum fused as directed with other sunprotection measures(see Directions)decreases the risk of skin cancer andeary skin aging caused by the sun

DOSAGE AND ADMINISTRATION

Apoly liberally i5 mnutes before sunexoosure.pants, hats andsunglasses. Children under 6months of age: ask a doctor
Reapph: Aler 80 minues oswinming or sneaing immetlaletater ionel dning Atleast eveny2hours.Sun precion leasures Spending ime in the sun increasesyour isk oifshincancer and eaty skinaging T
decrease this rsk requlanuse a sunsren uith a bradspecnum spf value of 15 or higtherAnd ohersun prolecion measureshclud ng imtime ihthe sun especdaly fom 10am.2am.

INDICATIONS AND USAGE

Apoly liberally i5 mnutes before sunexoosure.pants, hats andsunglasses. Children under 6months of age: ask a doctor
Reapph: Aler 80 minues oswinming or sneaing immetlaletater ionel dning Atleast eveny2hours.Sun precion leasures Spending ime in the sun increasesyour isk oifshincancer and eaty skinaging T
decrease this rsk requlanuse a sunsren uith a bradspecnum spf value of 15 or higtherAnd ohersun prolecion measureshclud ng imtime ihthe sun especdaly fom 10am.2am.

Keep out of reach of children. lf swallowed, get medical help or contact a Poison Control Center right away

OTHER SAFETY INFORMATION

Protect this product in this container from excessive heat and direct sun.

INACTIVE INGREDIENT

Vinyl Dimethicone/Methicone Silsesquioxane Crosspolymer
Aluminum hydroxide
Mica
Lophatherum Gracile Leaf
Dimethicone
Triethoxycaprylylsilane
Stearic Acid
Tocopherol
CI 77492
CI 77491
Sodium Benzoate
Potassium Sorbate
Daucus Carota Sativa (Carrot) Seed Oil
Lavandula Angustifolia (Lavender) Oil

WARNINGS

For enemal use onyDo nd use on damaged or icken shnwmen using his poductkep ou oeyes Rise wth walerto remove slop use and ask adoco lrash occursKeep out d reachof thilien. producs
swallowed. get medical helpor contact a Potson Control Center rightaway